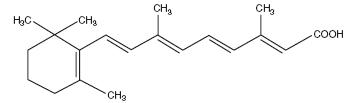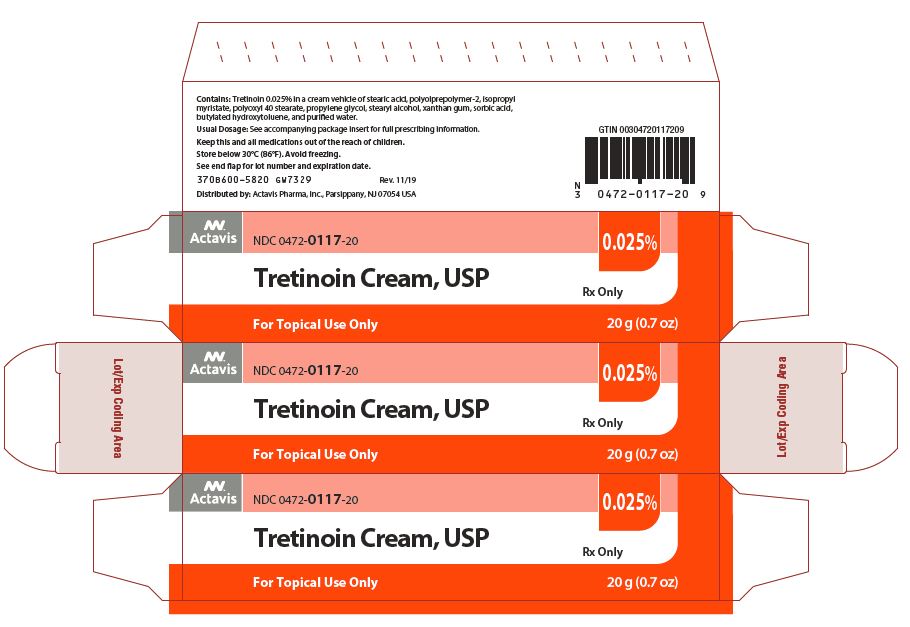 DRUG LABEL: Tretinoin
NDC: 0472-0117 | Form: CREAM
Manufacturer: Actavis Pharma, Inc.
Category: prescription | Type: HUMAN PRESCRIPTION DRUG LABEL
Date: 20241211

ACTIVE INGREDIENTS: TRETINOIN 0.25 mg/1 g
INACTIVE INGREDIENTS: STEARIC ACID; PPG-12/SMDI COPOLYMER; ISOPROPYL MYRISTATE; POLYOXYL 40 STEARATE TYPE I; PROPYLENE GLYCOL; STEARYL ALCOHOL; XANTHAN GUM; SORBIC ACID; BUTYLATED HYDROXYTOLUENE; WATER

TRETINOIN CREAM USP, 0.025%

FOR TOPICAL USE ONLY

Rx Only

DESCRIPTION

Tretinoin Cream, USP a topical retinoid, contains tretinoin USP, 0.025% by weight in a hydrophilic cream vehicle of stearic acid, polyolprepolymer-2, isopropyl myristate, polyoxyl 40 stearate, propylene glycol, stearyl alcohol, xanthan gum, sorbic acid, butylated hydroxytoluene, and purified water. Chemically, tretinoin is all-trans-retinoic acid (C20H2802; molecular weight 300.44 vitamin A acid) and has the following structural formula:

CLINICAL PHARMACOLOGY

Although the exact mode of action of tretinoin is unknown, current evidence suggests that topical tretinoin decreases cohesiveness of follicular epithelial cells with decreased microcomedo formation. Additionally, tretinoin stimulates mitotic activity and increased turnover of follicular epithelial cells causing extrusion of the comedones.

Pharmacokinetics:

In vitro and in vivo pharmacokinetic studies with tretinoin cream indicate that less than 0.3% of the topically applied dose is bioavailable. Circulating plasma levels of both tretinoin and isotretinoin are only slightly elevated above those found in healthy normal controls.

CLINICAL STUDIES

In one vehicle-controlled clinical trial, Tretinoin Cream 0.025%, applied once daily was more effective than vehicle in the treatment of facial acne vulgaris of mild to moderate severity. Percent reductions in lesion count after treatment for 12 weeks in this study are shown in the following table:

 | Tretinoin Cream, | Vehicle
 | 0.025% | Cream
 | N = 75 | N = 58
Noninflammatory Lesions | 45% | 27%
Inflammatory Lesions | 46% | 32%
Total Lesions | 46% | 28%
N = Number of Subjects

INDICATIONS AND USAGE

Tretinoin Cream, USP is indicated for topical application in the treatment of acne vulgaris. The safety and efficacy of this product in the treatment of other disorders have not been established.

CONTRAINDICATIONS

The product should not be used if there is hypersensitivity to any of the ingredients.

PRECAUTIONS

General

If a reaction suggesting sensitivity or chemical irritation occurs, use of the medication should be discontinued. Exposure to sunlight, including sunlamps or artificial sunlight, should be minimized during the use of tretinoin cream, and patients with sunburn should be advised not to use the product until fully recovered because of heightened susceptibility to sunlight as a result of the use of tretinoin. Patients who may be required to have considerable sun exposure due to occupation and those with inherent sensitivity to the sun should exercise particular caution. Use of sunscreen products and protective clothing over treated areas is recommended when exposure cannot be avoided. Weather extremes, such as wind or cold, also may be irritating to patients under treatment with tretinoin.

Tretinoin Cream, 0.025% should be kept away from the eyes, the mouth, the paranasal creases, and mucous membranes. Topical use may induce severe local erythema and peeling at the site of application. If the degree of local irritation warrants, patients should be directed to temporarily use the medication less frequently, discontinue use temporarily, or discontinue use altogether. Efficacy at reduced frequencies of application has not been established. Tretinoin has been reported to cause severe irritation on eczematous skin and should be used with utmost caution in patients with this condition.

Information for Patients

See attached Patient Package Insert.

Drug Interactions

Concomitant topical medication, medicated or abrasive soaps and cleansers, soaps and cosmetics that have a strong drying effect, and products with high concentrations of alcohol, astringents, spices or lime should be used with caution because of possible interaction with tretinoin. Particular caution should be exercised in using preparations containing sulfur, resorcinol, or salicylic acid with tretinoin cream. It also is advisable to “rest” a patient’s skin until the effects of such preparations subside before use of tretinoin cream is begun.

Carcinogenesis, Mutagenesis and Impairment of Fertility

In a life-time dermal study in CD-1 mice with another tretinoin cream, at 100 and 200 times the average recommended human topical clinical dose, a few skin tumors in the female mice and liver tumors in male mice were observed. The biological significance of these findings is not clear because they occurred at doses that exceeded the dermal maximally tolerated dose (MTD) of tretinoin and because they were within the background natural occurrence rate for these tumors in this strain of mice. There was no evidence of carcinogenic potential when tretinoin was administered topically at a dose five times the average recommended human topical clinical dose. For purposes of comparisons of the animal exposure to human exposure, the “recommended human topical clinical dose” is defined as 1.0 g of 0.025% Tretinoin Cream applied daily to a 50 kg person. In a chronic, two-year bioassay of vitamin A acid in mice performed by Tsubura and Yamamoto, generalized amyloid deposition was reported in all vitamin A treated groups in the basal layer of the skin. In CD-1 mice, a similar study reported hyalinization at the treated skin sites and the incidence of this finding was 0/50, 3/50, 3/50, and 2/50 in male mice and 1/50, 0/50, 4/50, and 2/50 in female mice from the vehicle control, 0.25 mg/kg, 0.5 mg/kg, and 1 mg/kg groups, respectively.

Studies in hairless albino mice suggest that tretinoin may enhance the tumorigenic potential of carcinogenic doses of UVB and UVA light from a solar simulator. In other studies, when lightly pigmented hairless mice treated with tretinoin were exposed to carcinogenic doses of UVA/UVB light, the incidence and rate of development of skin tumors were either reduced or no effect was seen. Due to significantly different experimental conditions, no strict comparison of these disparate data is possible at this time. Although the significance of these studies to humans is not clear, patients should minimize exposure to sun.

The mutagenic potential of tretinoin was evaluated in the Ames assay and in the in vivo mouse micronucleus assay, both of which were negative.

Dermal Segment I and III studies with tretinoin cream have not been performed in any species. In oral Segment I and Segment III studies in rats with tretinoin, decreased survival of neonates and growth retardation were observed at doses in excess of 2 mg/kg/day (> 400 times the average recommended human topical clinical dose).

Pregnancy:

Teratogenic Effects

Oral tretinoin has been shown to be teratogenic in rats, mice, rabbits, hamsters, and subhuman primates. It was teratogenic and fetotoxic in rats when given orally in doses 1000 times the average recommended human topical clinical dose. However, variations in teratogenic doses among various strains of rats have been reported. In the cynomolgus monkey, which metabolically is closer to humans for tretinoin than other species examined, fetal malformations were reported at oral doses of 10 mg/kg/day or greater, but none were observed at 5 mg/kg/day (1000 times the average recommended human topical clinical dose), although increased skeletal variations were observed at all doses. Dose-related increased embryolethality and abortion were reported. Similar results have also been reported in pigtail macaques.

Topical tretinoin in animal teratogenicity tests has generated equivocal results. There is evidence for teratogenicity (shortened or kinked tail) of topical tretinoin in Wistar rats at doses greater than 1 mg/kg/day (200 times the recommended human topical clinical dose). Anomalies (humerus: short 13%, bent 6%; os parietal incompletely ossified 14%) have also been reported in rats when 10 mg/kg/day was dermally applied.

Topical tretinoin (Tretinoin Cream, 0.1%) has been shown to be teratogenic in rabbits when given in doses 91 times the topical human dose for cream (assuming a 50 kg adult applies 1.0 g of 0.1% cream topically). In this study, increased incidence of cleft palate and hydrocephaly was reported in the tretinoin-treated animals.

There are other reports, in New Zealand White rabbits with doses of approximately 80 times the recommended human topical clinical dose, of an increased incidence of domed head and hydrocephaly, typical of retinoid-induced fetal malformations in this species.

When given subcutaneously to rabbits, tretinoin was teratogenic at 2 mg/kg/day but not at 1 mg/kg/day. These doses are approximately 400 and 200 times, respectively, the human topical dose of tretinoin cream, 0.025% (assuming a 50 kg adult applies 1.0 g of 0.025% cream topically).

In contrast, several well-controlled animal studies have shown that dermally applied tretinoin was not teratogenic at doses of 100 and 200 times the recommended human topical clinical dose, in rats and rabbits, respectively.

With widespread use of any drug, a small number of birth defect reports associated temporally with the administration of the drug would be expected by chance alone. Thirty cases of temporally associated congenital malformations have been reported during two decades of clinical use of another formulation of topical tretinoin (Retin-A). Although no definite pattern of teratogenicity and no causal association have been established from these cases, five of the reports describe the rare birth defect category, holoprosencephaly (defects associated with incomplete midline development of the forebrain). The significance of these spontaneous reports in terms of risk to the fetus is not known.

Nonteratogenic Effects

Dermal tretinoin has been shown to be fetotoxic in rabbits when administered in doses 100 times the recommended topical human clinical dose. Oral tretinoin has been shown to be fetotoxic in rats when administered in doses 500 times the recommended topical human clinical dose. There are, however, no adequate and well-controlled studies in pregnant women. Tretinoin Cream, 0.025% should not be used during pregnancy.

Nursing Mothers

It is not known whether this drug is excreted in human milk. Because many drugs are excreted in human milk, caution should be exercised when tretinoin cream is administered to a nursing woman.

ADVERSE REACTIONS

The skin of certain sensitive individuals may become excessively red, edematous, blistered, or crusted. If these effects occur, the medication should either be discontinued until the integrity of the skin is restored, or the medication dosing frequency should be adjusted temporarily to a level the patient can tolerate. However, efficacy has not been established for lower dosing frequencies. True contact allergy to topical tretinoin is rarely encountered. Temporary hyper- or hypopigmentation has been reported with repeated application of tretinoin cream. Some individuals have been reported to have heightened susceptibility to sunlight while under treatment with tretinoin cream. Adverse effects of tretinoin cream have been reversible upon discontinuation of therapy (see DOSAGE AND ADMINISTRATION section).

OVERDOSAGE

If medication is applied excessively, no more rapid or better results will be obtained and marked redness, peeling, or discomfort may occur. Oral ingestion of the drug may lead to the same side effects as those associated with excessive oral intake of vitamin A.

DOSAGE AND ADMINISTRATION

Tretinoin Cream should be applied once a day, in the evening, to the skin where acne lesions appear, using enough to cover the entire affected area lightly. Application may cause a transient feeling of warmth or slight stinging. In cases where it has been necessary to temporarily discontinue therapy or reduce the frequency of application, therapy may be resumed or frequency of application increased when the patients become able to tolerate the treatment. Alterations of dose frequency should be closely monitored by careful observation of the clinical therapeutic response and skin tolerance. Efficacy has not been established for less than once-daily dosing frequencies.

During the early weeks of therapy, an apparent increase in number and exacerbation of inflammatory acne lesions may occur. This is due, in part, to the action of the medication on deep, previously unseen lesions and should not be considered a reason to discontinue therapy. Therapeutic results should be noticed after two to three weeks but more than six weeks of therapy may be required before definite beneficial effects are seen.

Patients treated with tretinoin cream may use cosmetics, but the areas to be treated should be cleansed thoroughly before the medication is applied (see PRECAUTIONS section).

HOW SUPPLIED

Tretinoin Cream USP, 0.025% is supplied in 20 g (NDC 0472-0117-20) and 45 g (NDC 0472-0117-45) tubes.

Storage Conditions: Store below 30°C (86°F). Avoid freezing.

Keep this and all medications out of the reach of children.

Distributed by:
Actavis Pharma, Inc.
Parsippany, NJ 07054 USA

Revised - November 2019

PATIENT INSTRUCTIONS

TRETINOIN CREAM USP, 0.025%

Acne Treatment

IMPORTANT

Read Directions Carefully Before Using

THIS LEAFLET TELLS YOU ABOUT TRETINOIN CREAM ACNE TREATMENT AS PRESCRIBED BY YOUR PHYSICIAN. THIS PRODUCT IS TO BE USED ONLY ACCORDING TO YOUR DOCTOR’S INSTRUCTIONS, AND IT SHOULD NOT BE APPLIED TO OTHER AREAS OF THE BODY OR TO OTHER GROWTHS OR LESIONS. THE SAFETY AND EFFECTIVENESS OF THIS PRODUCT IN OTHER DISORDERS HAVE NOT BEEN EVALUATED. IF YOU HAVE ANY QUESTIONS, BE SURE TO ASK YOUR DOCTOR.

PRECAUTIONS

The effects of the sun on your skin: As you know, overexposure to natural sunlight or the artificial sunlight of a sunlamp can cause sunburn. Overexposure to the sun over many years may cause premature aging of the skin and even skin cancer. The chances of these effects occurring will vary depending on skin type, the climate and the care taken to avoid overexposure to the sun. Therapy with tretinoin cream may make your skin more susceptible to sunburn and other adverse effects of the sun, so unprotected exposure to natural or artificial sunlight should be minimized.

Laboratory findings: When laboratory mice are exposed to artificial sunlight, they often develop skin tumors. These sunlight-induced tumors may appear more quickly and in greater number if the mouse is also topically treated with the active ingredient in tretinoin cream, tretinoin. In some studies, under different conditions, however, when mice treated with tretinoin were exposed to artificial sunlight, the incidence and rate of development of skin tumors were reduced. There is no evidence to date that tretinoin alone will cause the development of skin tumors in either laboratory animals or humans. However, investigations in this area are continuing.

Use caution in the sun: When outside, even on hazy days, areas treated with tretinoin cream should be protected. An effective sunscreen should be used any time you are outside (consult your physician for a recommendation of an SPF level which will provide you with the necessary high level of protection). For extended sun exposure, protective clothing, like a hat, should be worn. Do not use artificial sunlamps or artificial sunlight while you are using Tretinoin Cream, 0.025%. If you do become sunburned, stop your therapy with tretinoin cream until your skin has recovered.

Avoid excessive exposure to wind or cold: Extremes of climate tend to dry or burn normal skin. Skin treated with tretinoin cream may be more vulnerable to these extremes. Your physician can recommend ways to manage your acne treatment under such conditions.

Possible problems: The skin of certain sensitive individuals may become excessively red, swollen, blistered, or crusted. If you are experiencing severe or persistent irritation, discontinue the use of tretinoin cream and consult your physician.

There have been reports that, in some patients, areas treated with tretinoin cream developed a temporary increase or decrease in the amount of skin pigment (color) present.

Use other medication only on your physician’s advice: Only your physician knows which other medications may be helpful during treatment and will recommend them to you if necessary. Follow the physician’s instructions carefully. In addition, you should avoid preparations that may dry or irritate your skin. These preparations may include certain astringents, toiletries containing alcohol, spices or lime, or certain medicated soaps, shampoos, and hair permanent solutions. Do not allow anyone else to use this medication.

Do not use other medications with tretinoin cream which are not recommended by your doctor. The medications you have used in the past might cause unnecessary redness or peeling.

If you are pregnant, think you are pregnant, or are nursing an infant: No studies have been conducted in humans to establish the safety of tretinoin cream in pregnant women. If you are pregnant, think you are pregnant, or are nursing a baby, consult your physician before using this medication.

AND WHILE YOU’RE ON TRETINOIN THERAPY

Use a mild non-medicated soap. Avoid frequent washings and harsh scrubbing. Acne isn’t caused by dirt, so no matter how hard you scrub, you can’t wash it away. Washing too frequently or scrubbing too roughly may at times actually make your acne worse. Wash your skin gently with a mild, bland soap. Two or three times a day should be sufficient. Pat skin dry with a towel. Let the face dry 20 to 30 minutes before applying Tretinoin Cream, 0.025%. Remember, excessive irritation such as rubbing, too much washing, use of other medications not suggested by your physician, etc., may worsen your acne.

HOW TO USE TRETINOIN CREAM

To get the best results with tretinoin cream therapy, it is necessary to use it properly. Forget about the instructions given for other products and the advice of friends. Just stick to the special plan your doctor has laid out for you and be patient. Remember, when tretinoin cream is used properly, many users see improvement by 12 weeks.

AGAIN, FOLLOW INSTRUCTIONS - BE PATIENT - DON’T START AND STOP THERAPY ON YOUR OWN - IF YOU HAVE QUESTIONS, ASK YOUR DOCTOR.

To help you use the medication correctly, keep these simple instructions in mind.

- Tretinoin cream should be applied once a day, in the evening, or as directed by your physician, to the skin where acne lesions appear, using enough to cover the entire affected area lightly. First, wash with a mild soap and dry your skin gently. WAIT 20 to 30 MINUTES BEFORE APPLYING MEDICATION; it is important for skin to be completely dry in order to minimize possible irritation.
- It is better not to use more than the amount suggested by your physician or to apply more frequently than instructed. Too much may irritate the skin, waste medication, and won’t give faster or better results.
- Keep the medication away from the corners of the nose, mouth, eyes, and open wounds. Spread away from these areas when applying.
- Cream: Squeeze about a half inch or less of medication onto the fingertip. While that should be enough for your whole face, after you have had some experience with the medication you may find you need slightly more or less to do the job. The medication should become invisible almost immediately. If it is still visible, you are using too much. Cover the affected area lightly with tretinoin cream by first dabbing it on your forehead, chin, and both cheeks, then spreading it over the entire affected area. Smooth gently into the skin.
- If needed, you may apply a moisturizer or a moisturizer with sunscreen that will not aggravate your acne (noncomedogenic) in the morning after you wash.

WHAT TO EXPECT WITH YOUR NEW TREATMENT

Tretinoin Cream, 0.025% works deep inside your skin and this takes time. You cannot make tretinoin cream work any faster by applying more than one dose each day, but an excess amount of tretinoin cream may irritate your skin. Be patient.

There may be some discomfort or peeling during the early days of treatment. Some patients also notice that their skin begins to take on a blush.

These reactions do not happen to everyone. If they do, it is just your skin adjusting to tretinoin cream and this usually subsides within two to four weeks. These reactions can usually be minimized by following instructions carefully. Should the effects become excessively troublesome, consult your doctor.

BY THREE TO SIX WEEKS, some patients notice an appearance of new blemishes (papules and pustules). At this stage, it is important to continue using tretinoin cream.

If tretinoin cream is going to have a beneficial effect for you, you should notice an improvement in your appearance by 6 to 12 weeks of therapy. Don’t be discouraged if you see no immediate improvement. Don’t stop treatment at the first signs of improvement.

Once your acne is under control, you should continue regular application of tretinoin cream until your physician instructs otherwise.

Call your doctor for medical advice about side effects. You may report side effects to FDA at 1-800-FDA-1088.

Distributed by:
Actavis Pharma, Inc.
Parsippany, NJ 07054 USA

Revised - November 2019

PACKAGE LABEL.PRINCIPAL DISPLAY PANEL

Actavis

NDC 0472-0117-20

Tretinoin Cream, USP 0.025%

Rx Only

For Topical Use Only

20 g (0.7 oz)